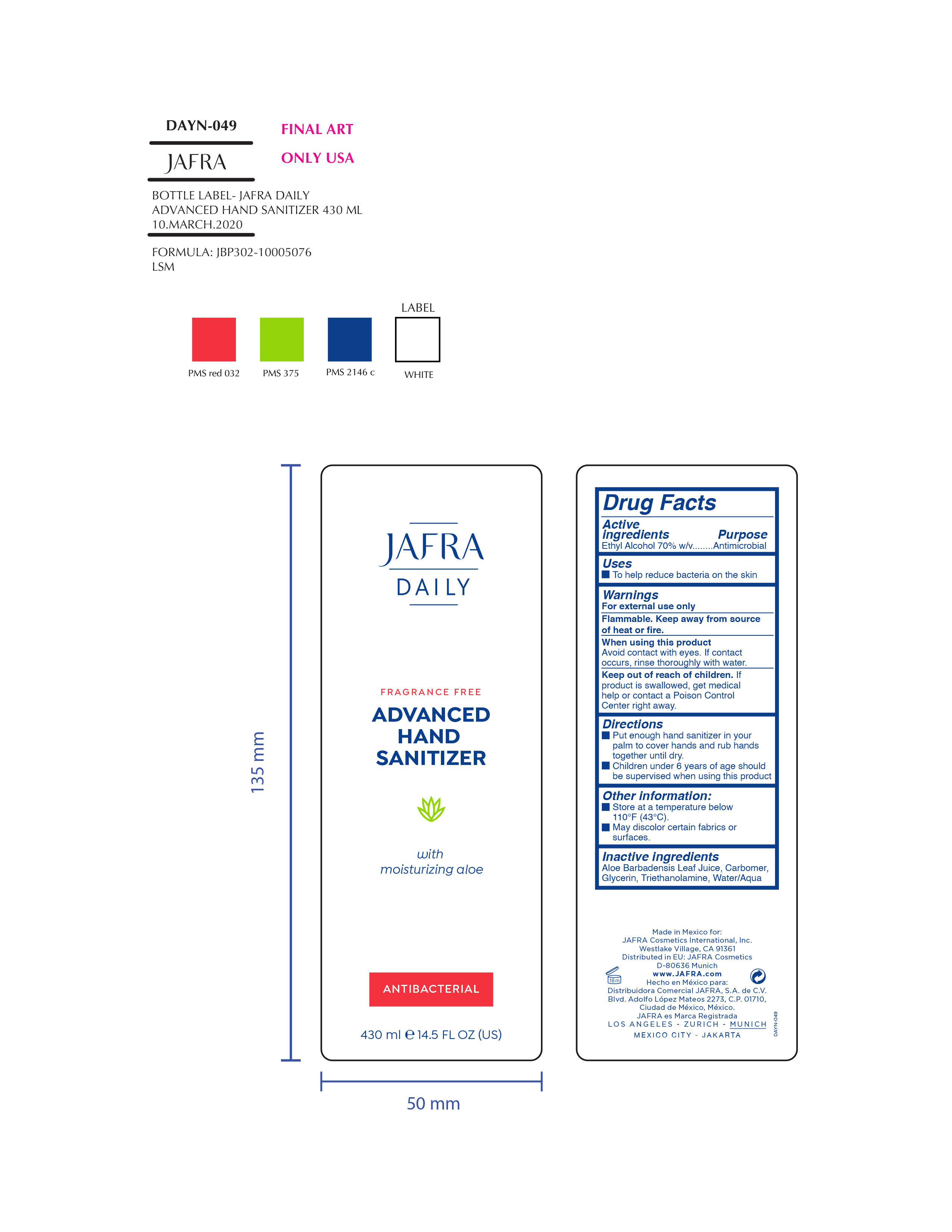 DRUG LABEL: Jafra Daily Advanced Hand Sanitizer
NDC: 68828-287 | Form: SOLUTION
Manufacturer: Jafra Cosmetics International Inc
Category: otc | Type: HUMAN OTC DRUG LABEL
Date: 20200330

ACTIVE INGREDIENTS: ALCOHOL 70 g/100 mL
INACTIVE INGREDIENTS: CARBOMER HOMOPOLYMER, UNSPECIFIED TYPE; ALOE VERA LEAF; TROLAMINE; GLYCERIN; WATER

Jafra Daily Advanced Hand Sanitizer

Active ingredients Purpose:

Ethyl Alcohol 70% w/v. Antimicrobial

Uses

- To help reduce bacteria on the skin

Keep out of reach of children. If product is swallowed, get medical help or contact a Poison Control Center right away.

When using this product

Avoid contact with eyes. If contact occurs rinse thoroughly with water.

WARNINGS

For external use only.

Flammable. Keep away from source of heat or flame.

When using this product keep out of eyes, ears, and mouth. In case of contact with eyes, rinse eyes thoroughly with water.
Stop use and ask a doctor if irritation or rash occurs. These may be signs of a serious condition.
Keep out of reach of children. If swallowed, get medical help or contact a Poison Control Center right away.

Directions

- Place enough product on hands to cover all surfaces. Rub hands together until dry.
- Supervise children under 6 years of age when using this product to avoid swallowing.

Inactive ingredients

Aloe Barbadensis Leaf Juice, Carbomer, Glycerin, Triethanolamine, Water/Aqua

PACKAGE LABEL

Jafra Daily

Fragrance Free

Advanced Hand Sanitizer

with moisturizing aloe

Antibacterial

430 ml e 14.5 FL Oz (US)